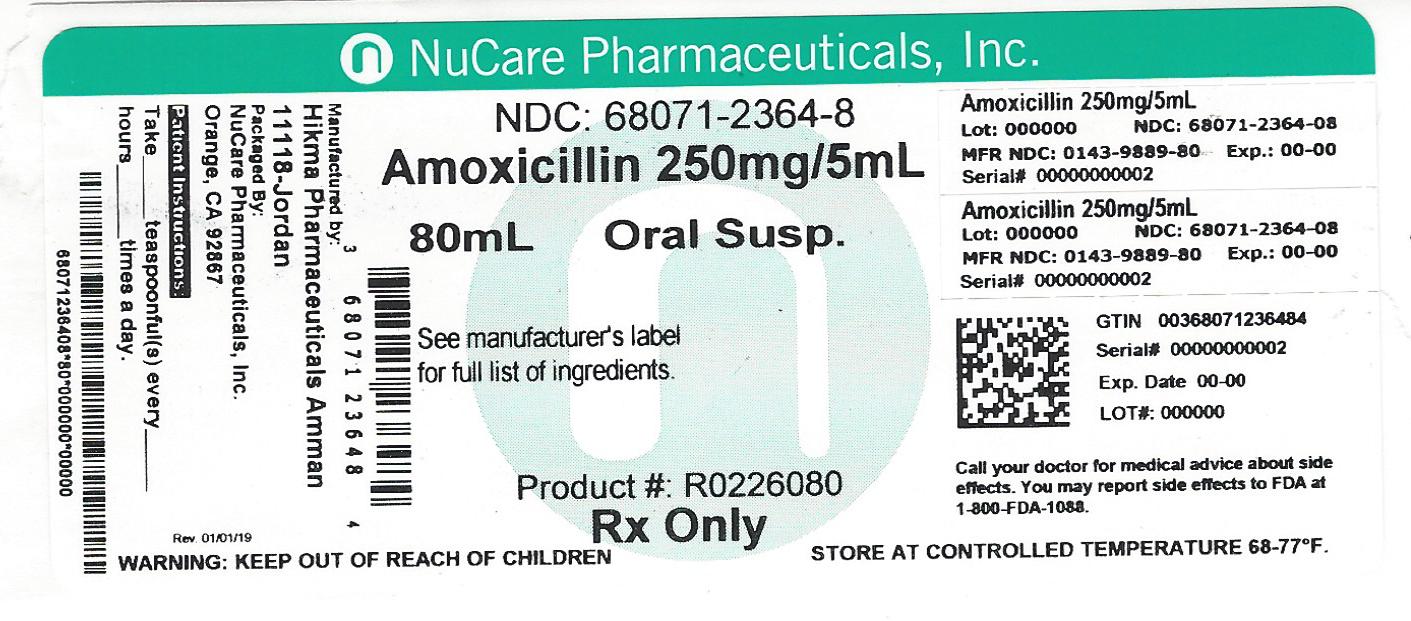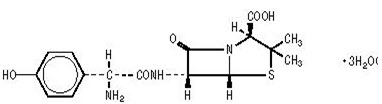 DRUG LABEL: Amoxicillin
NDC: 68071-2364 | Form: POWDER, FOR SUSPENSION
Manufacturer: NuCare Pharmaceuticals,Inc.
Category: prescription | Type: HUMAN PRESCRIPTION DRUG LABEL
Date: 20260219

ACTIVE INGREDIENTS: AMOXICILLIN 250 mg/5 mL
INACTIVE INGREDIENTS: SILICON DIOXIDE; HYPROMELLOSES; SODIUM BENZOATE; SUCROSE; TRISODIUM CITRATE DIHYDRATE; XANTHAN GUM

HIGHLIGHTS OF PRESCRIBING INFORMATION

These highlights do not include all the information needed to use AMOXICILLIN for Oral Suspension safely and effectively. See full prescribing information for AMOXICILLIN for Oral Suspension.
AMOXICILLIN for Oral Suspension for oral use
Dye free
Rx Only
Initial U.S. Approval: 1974
To reduce the development of drug-resistant bacteria and maintain the effectiveness of AMOXICILLIN and other antibacterial drugs, AMOXICILLIN should be used only to treat infections that are proven or strongly suspected to be caused by bacteria.

1 INDICATIONS AND USAGE

Amoxicillin for Oral Suspension is a penicillin-class antibacterial indicated for treatment of infections due to susceptible strains of designated microorganisms.
• Infections of the ear, nose, throat, genitourinary tract, skin and skin structure, and lower respiratory tract. (1.1 – 1.5)
• In combination for treatment of H. pylori infection and duodenal ulcer disease. (1.6, 1.7)

2 DOSAGE AND ADMINISTRATION

- In adults, 750-1750 mg/day in divided doses every 8-12 hours. In Pediatric Patients > 3 Months of Age, 20-45 mg/kg/day in divided doses every 8-12 hours. Refer to full prescribing information for specific dosing regimens. (2.1, 2.2, 2.3)
- Treatment of gonorrhea is 3 grams as a single oral dose. (2.1)
- The upper dose for neonates and infants ≤ 3 months is 30 mg/kg/day divided every 12 hours. (2.2)
- Dosing for H. pylori Infection: Triple therapy: 1 gram Amoxicillin, 500 mg clarithromycin, and 30 mg lansoprazole, all given twice daily (every 12 hours) for 14 days. Dual therapy: 1 gram Amoxicillin and 30 mg lansoprazole, each given three times daily (every 8 hours) for 14 days. (2.3)
- Reduce the dose in patients with severe renal impairment (GFR <30 mL/min). (2.4)

3 DOSAGE FORMS AND STRENGTHS

- for Oral Suspension: 125 mg/5 mL, 200 mg/5 mL, 250 mg/5 mL, 400 mg/5 mL (3)

4 CONTRAINDICATIONS

- History of a serious hypersensitivity reaction (e.g., anaphylaxis or Stevens-Johnson syndrome) to Amoxicillin or to other beta-lactams (e.g., penicillins or cephalosporins) (4).

5 WARNINGS AND PRECAUTIONS

- Anaphylactic reactions: Serious and occasionally fatal anaphylactic reactions have been reported in patients on penicillin therapy. Serious anaphylactic reactions require immediate emergency treatment with supportive measures. (5.1)
- Clostridium difficile-associated diarrhea (ranging from mild diarrhea to fatal colitis): Evaluate if diarrhea occurs. (5.2)

6 ADVERSE REACTIONS

The most common adverse reactions (> 1%) observed in clinical trials of Amoxicillin for oral suspension were diarrhea, rash, vomiting, and nausea. (6.1)

To report SUSPECTED ADVERSE REACTIONS, contact West-Ward Pharmaceutical Corp. at 1-877-233-2001, or the FDA at 1-800-FDA-1088 or www.fda.gov/medwatch.

7 DRUG INTERACTIONS

- Probenicid decreases renal tubular secretion of Amoxicillin which may result in increased blood levels of Amoxicillin. (7.1)
- Concomitant use of Amoxicillin and oral anticoagulants may increase the prolongation of prothrombin time. (7.2)
- Coadministration with allopurinol increases the risk of rash. (7.3)
- Amoxicillin may reduce the efficacy of oral contraceptives. (7.4)

8 USE IN SPECIFIC POPULATIONS

- Pediatric: Modify dose in patients 12 weeks or younger (≤ 3 months).(8.4)

FULL PRESCRIBING INFORMATION

1 INDICATIONS AND USAGE

To reduce the development of drug-resistant bacteria and maintain the effectiveness of Amoxicillin and other antibacterial drugs, Amoxicillin for Oral Suspension should be used only to treat infections that are proven or strongly suspected to be caused by bacteria. When culture and susceptibility information are available, they should be considered in selecting or modifying antibacterial therapy. In the absence of such data, local epidemiology and susceptibility patterns may contribute to the empiric selection of therapy.

Amoxicillin for Oral Suspension is indicated in the treatment of infections due to susceptible (ONLY β-lactamase–negative) isolates of the designated bacteria in the conditions listed below:

1.1 Infections of the ear, nose, and throat

- due to Streptococcus species.(α- and β-hemolytic isolates only), Streptococcus pneumoniae, Staphylococcus spp., or Haemophilus influenzae.

1.2 Infections of the genitourinary tract

- due to Escherichia coli, Proteus mirabilis, or Enterococcus faecalis.

1.3 Infections of the skin and skin structure

- due to Streptococcus spp.
(α- and β-hemolytic isolates only), Staphylococcus spp., or E. coli.

1.4 Infections of the lower respiratory tract

- due to Streptococcus spp.
(α- and β-hemolytic isolates only), S. pneumoniae, Staphylococcus spp., or H. influenzae.

1.5 Gonorrhea, acute uncomplicated (ano-genital and urethral infections in males and females)

- due to Neisseria gonorrhoeae.
Because of high rates of Amoxicillin resistance, Amoxicillin for Oral Suspension is not recommended for empiric treatment of gonorrhea. Amoxicillin for Oral Suspension use should be limited to situations where N. gonorrhoeae isolates are known to be susceptible to Amoxicillin.

1.6 Triple therapy for Helicobacter pylori with clarithromycin and lansoprazole:

Amoxicillin for Oral Suspension in combination with clarithromycin plus lansoprazole as triple therapy, is indicated for the treatment of patients with H. pylori infection and duodenal ulcer disease (active or 1-year history of a duodenal ulcer) to eradicate H. pylori. Eradication of H. pylori has been shown to reduce the risk of duodenal ulcer recurrence.

1.7 Dual therapy for H. pylori with lansoprazole

Amoxicillin for Oral Suspension, in combination with lansoprazole delayed-release capsules as dual therapy, is indicated for the treatment of patients with H. pylori infection and duodenal ulcer disease (active or 1-year history of a duodenal ulcer) who are either allergic or intolerant to clarithromycin or in whom resistance to clarithromycin is known or suspected. (See the clarithromycin package insert, MICROBIOLOGY.) Eradication of H. pylori has been shown to reduce the risk of duodenal ulcer recurrence.

2 DOSAGE AND ADMINISTRATION

2.1 Dosing for Adult and Pediatric Patients > 3 Months of Age

Except for gonorrhea, treatment should be continued for a minimum of 48 to 72 hours beyond the time that the patient becomes asymptomatic or evidence of bacterial eradication has been obtained. It is recommended that there be at least 10 days’ treatment for any infection caused by Streptococcus pyogenes to prevent the occurrence of acute rheumatic fever. In some infections, therapy may be required for several weeks. It may be necessary to continue clinical and/or bacteriological follow-up for several months after cessation of therapy.

Infection | Severitya | Usual Adult Dose | Usual Dose for Children > 3 Monthsb
Ear/Nose/Throat Skin/ Skin Structure Genitourinary Tract | Mild/ Moderate | 500 mg every 12 hours or 250 mg every 8 hours | 25 mg/kg/day in divided doses every 12 hours or 20 mg/kg/day in divided doses every 8 hours
Ear/Nose/Throat Skin/ Skin Structure Genitourinary Tract | Severe | 875 mg every 12 hours or 500 mg every 8 hours | 45 mg/kg/day in divided doses every 12 hours or 40 mg/kg/day in divided doses every 8 hours
Lower Respiratory Tract | Mild/ Moderate or Severe | 875 mg every 12 hours or 500 mg every 8 hours | 45 mg/kg/day in divided doses every 12 hours or 40 mg/kg/day in divided doses every 8 hours
Gonorrhea Acute, uncomplicated ano-genital and urethral infections in males and females |  | 3 grams as single oral dose | Prepubertal children: 50 mg/kg Amoxicillin, combined with 25 mg/kg probenecid as a single dose. Note: since probenecid is contraindicated in children under 2 years, do not use this regimen in children under 2 years of age.

a Dosing for infections caused by bacteria that are intermediate in their susceptibility to Amoxicillin should follow the recommendations for severe infections.
b The children’s dosage is intended for individuals whose weight is less than 40 kg. Children weighing 40 kg or more should be dosed according to the adult recommendations.

2.2 Dosing in Neonates and Infants Aged ≤ 12 Weeks (≤ 3 Months)

Treatment should be continued for a minimum of 48 to 72 hours beyond the time that the patient becomes asymptomatic or evidence of bacterial eradication has been obtained. It is recommended that there be at least 10 days’ treatment for any infection caused by Streptococcus pyogenes to prevent the occurrence of acute rheumatic fever. Due to incompletely developed renal function affecting elimination of Amoxicillin in this age group, the recommended upper dose of Amoxicillin 30 mg/kg/day divided every 12 hours. There are currently no dosing recommendations for pediatric patients with impaired renal function.

2.3 Dosing for H. pylori Infection

Triple therapy: The recommended adult oral dose is 1 gram Amoxicillin, 500 mg clarithromycin, and 30 mg lansoprazole, all given twice daily (every 12 hours) for 14 days.

Dual therapy: The recommended adult oral dose is 1 gram Amoxicillin and 30 mg lansoprazole, each given three times daily (every 8 hours) for 14 days.

Please refer to clarithromycin and lansoprazole full prescribing information.

2.4 Dosing in Renal Impairment

- Patients with impaired renal function do not generally require a reduction in dose unless the impairment is severe.
- Severely impaired patients with a glomerular filtration rate of < 30 mL/min. should not receive a 875-mg dose.
- Patients with a glomerular filtration rate of 10 to 30 mL/min should receive 500 mg or 250 mg every 12 hours, depending on the severity of the infection.
- Patients with a glomerular filtration rate less than 10 mL/min should receive 500 mg or 250 mg every 24 hours, depending on severity of the infection.
- Hemodialysis patients should receive 500 mg or 250 mg every 24 hours, depending on severity of the infection. They should receive an additional dose both during and at the end of dialysis.

2.5 Directions for Mixing Oral Suspension

Tap bottle until all powder flows freely. Add approximately 1/3 of the total amount of water for reconstitution (see Table 2) and shake vigorously to wet powder. Add remainder of the water and again shake vigorously.

Table 2. Amount of Water for Mixing Oral Suspension
Strength | Bottle Size | Amount of Water Required for Reconstitution
Oral Suspension 125 mg /5 mL | 80 mL | 66 mL
 | 100 mL | 83 mL
 | 150 mL | 125 mL
Oral Suspension 200 mg /5 mL | 50 mL | 39 mL
 | 75 mL | 59 mL
 | 100 mL | 78 mL
Oral Suspension 250 mg /5 mL | 80 mL | 59 mL
 | 100 mL | 73 ml
 | 150 mL | 110 mL
Oral Suspension 400 mg /5 mL | 50 mL | 34 mL
 | 75 mL | 51 mL
 | 100 mL | 68 mL

After reconstitution, the required amount of suspension should be placed directly on the child’s tongue for swallowing. Alternate means of administration are to add the required amount of suspension to formula, milk, fruit juice, water, ginger ale, or cold drinks. These preparations should then be taken immediately.

NOTE: SHAKE ORAL SUSPENSION WELL BEFORE USING. Keep bottle tightly closed. Any unused portion of the reconstituted suspension must be discarded after 14 days. Refrigeration is preferable, but not required.

3 DOSAGE FORMS AND STRENGTHS

Amoxicillin for Oral Suspension:125 mg/5 mL, 200 mg/5 mL, 250 mg/5 mL, 400 mg/5 mL. Each 5 mL of reconstituted fruity flavored suspension contains 125 mg, 200 mg, 250 mg or 400 mg Amoxicillin as the trihydrate.

4 CONTRAINDICATIONS

Amoxicillin is contraindicated in patients who have experienced a serious hypersensitivity reaction (e.g., anaphylaxis or Stevens-Johnson syndrome) to Amoxicillin or to other β-lactam antibiotics (e.g., penicillins and cephalosporins).

5 WARNINGS AND PRECAUTIONS

5.1 Anaphylactic Reactions

Serious and occasionally fatal hypersensitivity (anaphylactic) reactions have been reported in patients on penicillin therapy including Amoxicillin. Although anaphylaxis is more frequent following parenteral therapy, it has occurred in patients on oral penicillins. These reactions are more likely to occur in individuals with a history of penicillin hypersensitivity and/or a history of sensitivity to multiple allergens.
There have been reports of individuals with a history of penicillin hypersensitivity who have experienced severe reactions when treated with cephalosporins. Before initiating therapy with Amoxicillin, careful inquiry should be made regarding previous hypersensitivity reactions to penicillins, cephalosporins, or other allergens.

5.2 Clostridium difficile Associated Diarrhea

Clostridium difficile associated diarrhea (CDAD) has been reported with use of nearly all antibacterial agents, including Amoxicillin, and may range in severity from mild diarrhea to fatal colitis. Treatment with antibacterial agents alters the normal flora of the colon leading to overgrowth of C. difficile.
C. difficile produces toxins A and B which contribute to the development of CDAD. Hypertoxin-producing strains of C. difficile cause increased morbidity and mortality, as these infections can be refractory to antimicrobial therapy and may require colectomy. CDAD must be considered in all patients who present with diarrhea following antibacterial use. Careful medical history is necessary since CDAD has been reported to occur over 2 months after the administration of antibacterial agents.
If CDAD is suspected or confirmed, ongoing antibiotic use not directed against C. difficile may need to be discontinued. Appropriate fluid and electrolyte management, protein supplementation, antibiotic treatment of C. difficile, and surgical evaluation should be instituted as clinically indicated.

5.3 Potential for Microbial Overgrowth or Bacterial Resistance

The possibility of superinfections with fungal or bacterial pathogens should be considered during therapy.
If superinfections occur, Amoxicillin should be discontinued and appropriate therapy instituted.
Prescribing Amoxicillin either in the absence of a proven or strongly suspected bacterial infection is unlikely to provide benefit to the patient, and increases the risk of the development of drug-resistant bacteria.

5.4 Use in Patients With Mononucleosis

A high percentage of patients with mononucleosis who receive Amoxicillin develop an erythematous skin rash. Thus Amoxicillin should not be administered to patients with mononucleosis.

5.5 Phenylketonurics

The oral suspensions of Amoxicillin do not contain phenylalanine and can be used by phenylketonurics.

6 ADVERSE REACTIONS

The following are discussed in more detail in other sections of the labeling:
• Anaphylactic reactions [see Warnings and Precautions (5.1)]
• CDAD [see Warnings and Precautions (5.2)]

6.1 Clinical Trials Experience

Because clinical trials are conducted under widely varying conditions, adverse reaction rates observed in the clinical trials of a drug cannot be directly compared to rates in the clinical trials of another drug and may not reflect the rates observed in practice.

The most common adverse reactions (> 1%) observed in clinical trials of Amoxicillin for oral suspension were diarrhea, rash, vomiting, and nausea.

Triple therapy: The most frequently reported adverse events for patients who received triple therapy (Amoxicillin/clarithromycin/ lansoprazole) were diarrhea (7%), headache (6%), and taste perversion (5%).
Dual therapy:The most frequently reported adverse events for patients who received double therapy Amoxicillin/lansoprazole were diarrhea (8%) and headache (7%). For more information on adverse reactions with clarithromycin or lansoprazole, refer to the Adverse Reactions section of their package inserts.

6.2 Postmarketing or Other Experience

In addition to adverse events reported from clinical trials, the following events have been identified during postmarketing use of penicillins. Because they are reported voluntarily from a population of unknown size, estimates of frequency cannot be made. These events have been chosen for inclusion due to a combination of their seriousness, frequency of reporting, or potential causal connection to Amoxicillin.

- Infections and Infestations: Mucocutaneous candidiasis.
- Gastrointestinal: Black hairy tongue, and hemorrhagic/pseudomembranous colitis. Onset of pseudomembranous colitis symptoms may occur during or after antibacterial treatment [see Warnings and Precautions (5.2)].
- Hypersensitivity Reactions: Anaphylaxis [see Warnings and Precautions (5.1)]. Serum sickness–like reactions, erythematous maculopapular rashes, erythema multiforme, Stevens-Johnson syndrome, exfoliative dermatitis, toxic epidermal necrolysis, acute generalized exanthematous pustulosis, hypersensitivity vasculitis, and urticaria have been reported.
- Liver: A moderate rise in AST and/or ALT has been noted, but the significance of this finding is unknown. Hepatic dysfunction including cholestatic jaundice, hepatic cholestasis and acute cytolytic hepatitis have been reported.
- Renal: Crystalluria has been reported [see Overdosage (10)].
- Hemic and Lymphatic Systems: Anemia, including hemolytic anemia, thrombocytopenia, thrombocytopenic purpura, eosinophilia, leukopenia, and agranulocytosis have been reported. These reactions are usually reversible on discontinuation of therapy and are believed to be hypersensitivity phenomena.
- Central Nervous System: Reversible hyperactivity, agitation, anxiety, insomnia, confusion, convulsions, behavioral changes, and/or dizziness have been reported.
- Miscellaneous: Tooth discoloration (brown, yellow, or gray staining) has been reported. Most reports occurred in pediatric patients. Discoloration was reduced or eliminated with brushing or dental cleaning in most cases.

7 DRUG INTERACTIONS

7.1 Probenecid

Probenecid decreases the renal tubular secretion of Amoxicillin. Concurrent use of Amoxicillin and probenecid may result in increased and prolonged blood levels of Amoxicillin.

7.2 Oral Anticoagulants

Abnormal prolongation of prothrombin time (increased international normalized ratio [INR]) has been reported in patients receiving Amoxicillin and oral anticoagulants. Appropriate monitoring should be undertaken when anticoagulants are prescribed concurrently. Adjustments in the dose of oral anticoagulants may be necessary to maintain the desired level of anticoagulation.

7.3 Allopurinol

The concurrent administration of allopurinol and Amoxicillin increases the incidence of rashes in patients receiving both drugs as compared to patients receiving Amoxicillin alone. It is not known whether this potentiation of Amoxicillin rashes is due to allopurinol or the hyperuricemia present in these patients.

7.4 Oral Contraceptives

Amoxicillin may affect the gut flora, leading to lower estrogen reabsorption and reduced efficacy of combined oral estrogen/progesterone contraceptives.

7.5 Other Antibacterials

Chloramphenicol, macrolides, sulfonamides, and tetracyclines may interfere with the bactericidal effects of penicillin. This has been demonstrated in vitro; however, the clinical significance of this interaction is not well documented.

7.6 Effects on Laboratory Tests

High urine concentrations of ampicillin may result in false-positive reactions when testing for the presence of glucose in urine using CLINITEST® (manufactured by Miles, Inc.), Benedict’s Solution, or Fehling’s Solution. Since this effect may also occur with Amoxicillin, it is recommended that glucose tests based on enzymatic glucose oxidase reactions [such as CLINISTIX® (manufactured by Bayer Corporation)] be used.

Following administration of ampicillin or Amoxicillin to pregnant women, a transient decrease in plasma concentration of total conjugated estriol, estriol-glucuronide, conjugated estrone, and estradiol has been noted.

8 USE IN SPECIFIC POPULATIONS

8.1 Pregnancy

Teratogenic Effects: Pregnancy Category B. Reproduction studies have been performed in mice and rats at doses up to 2000 mg/kg (3 and 6 times the 3 g human dose, based on body surface area). There was no evidence of harm to the fetus due to Amoxicillin. There are, however, no adequate and well-controlled studies in pregnant women. Because animal reproduction studies are not always predictive of human response, Amoxicillin should be used during pregnancy only if clearly needed.

8.2 Labor and Delivery

Oral ampicillin is poorly absorbed during labor. It is not known whether use of Amoxicillin in humans during labor or delivery has immediate or delayed adverse effects on the fetus, prolongs the duration of labor, or increases the likelihood of the necessity for an obstetrical intervention.

8.3 Nursing Mothers

Penicillins have been shown to be excreted in human milk. Amoxicillin use by nursing mothers may lead to sensitization of infants. Caution should be exercised when Amoxicillin is administered to a nursing woman.

8.4 Pediatric Use

Because of incompletely developed renal function in neonates and young infants, the elimination of Amoxicillin may be delayed. Dosing of Amoxicillin should be modified in pediatric patients 12 weeks or younger (≤ 3 months). [See Dosage and Administration (2.2).]

8.5 Geriatric Use

An analysis of clinical studies of Amoxicillin was conducted to determine whether subjects aged 65 and over respond differently from younger subjects. These analyses have not identified differences in responses between the elderly and younger patients, but a greater sensitivity of some older individuals cannot be ruled out.
This drug is known to be substantially excreted by the kidney, and the risk of toxic reactions to this drug may be greater in patients with impaired renal function. Because elderly patients are more likely to have decreased renal function, care should be taken in dose selection, and it may be useful to monitor renal function.

8.6 Dosing in Renal Impairment

Amoxicillin is primarily eliminated by the kidney and dosage adjustment is usually required in patients with severe renal impairment (GFR <30 mL/min). See Dosing in Renal Impairment (2.4) for specific recommendations in patients with renal impairment.

10 OVERDOSAGE

In case of overdosage, discontinue medication, treat symptomatically, and institute supportive measures as required. A prospective study of 51 pediatric patients at a poison control center suggested that overdosages of less than 250 mg/kg of Amoxicillin are not associated with significant clinical symptoms. Interstitial nephritis resulting in oliguric renal failure has been reported in a small number of patients after overdosage with Amoxicillin^1.

Crystalluria, in some cases leading to renal failure, has also been reported after Amoxicillin overdosage in adult and pediatric patients. In case of overdosage, adequate fluid intake and diuresis should be maintained to reduce the risk of Amoxicillin crystalluria.

Renal impairment appears to be reversible with cessation of drug administration. High blood levels may occur more readily in patients with impaired renal function because of decreased renal clearance of Amoxicillin. Amoxicillin may be removed from circulation by hemodialysis.

11 DESCRIPTION

Formulations of Amoxicillin for Oral Suspension, USP contain Amoxicillin, a semisynthetic antibiotic, an analog of ampicillin, with a broad spectrum of bactericidal activity against many Gram-positive and Gram-negative microorganisms. Chemically, it is (2 S,5 R,6 R)-6-[(R)-(-)-2-amino-2-(p-hydroxyphenyl)acetamido]-3,3-dimethyl-7-oxo-4-thia-1-zabicyclo[3.2.0]heptane-2-carboxylic acid trihydrate. It may be represented structurally as:

The Amoxicillin molecular formula is C16H19N3O5S•3H2O, and the molecular weight is 419.45.

Amoxicillin for Oral Suspension, USP: Each 5 mL of reconstituted suspension contains 125 mg, 200 mg, 250 mg or 400 mg Amoxicillin as the trihydrate. Each 5 mL of the 125 mg, 200 mg, 250 mg and 400 mg reconstituted suspension contains 0.1898 mEq (4.3635 mg) of sodium. Inactive ingredients: colloidal silicon dioxide, hypromellose, sodium benzoate, sucrose, trisodium citrate dihydrate, tutti frutti flavor and xanthan gum.

12 CLINICAL PHARMACOLOGY

12.1 Mechanism of Action

Amoxicillin is an antibacterial drug. [see Microbiology (12.4)].

12.3 Pharmacokinetics

Absorption: Amoxicillin is stable in the presence of gastric acid and is rapidly absorbed after oral administration. The effect of food on the absorption of Amoxicillin from the tablets and suspension of Amoxicillin has been partially investigated; 400 mg and 875 mg formulations have been studied only when administered at the start of a light meal.

Orally administered doses of 250 mg and 500 mg Amoxicillin capsules result in average peak blood levels 1 to 2 hours after administration in the range of 3.5 mcg/mL to 5 mcg/mL and 5.5 mcg/mL to 7.5 mcg/mL, respectively.

Mean Amoxicillin pharmacokinetic parameters from an open, two-part, single-dose crossover bioequivalence study in 27 adults comparing 875 mg of Amoxicillin with 875 mg of Amoxicillin/clavulanate potassium showed that the 875 mg tablet of Amoxicillin produces an AUC0-∞ of 35.4 ± 8.1 mcg•hr/mL and a Cmax of 13.8 ± 4.1 mcg/mL. Dosing was at the start of a light meal following an overnight fast.

Orally administered doses of Amoxicillin suspension, 125 mg/5 mL and 250 mg/5 mL, result in average peak blood levels 1 to 2 hours after administration in the range of 1.5 mcg/mL to 3 mcg/mL and 3.5 mcg/mL to 5 mcg/mL, respectively.

Oral administration of single doses of 400 mg chewable tablets and 400 mg/5 mL suspension of Amoxicillin to 24 adult volunteers yielded comparable pharmacokinetic data:

Table 3: Mean Pharmacokinetic Parameters of Amoxicillin (400 mg chewable tablets and 400 mg/5 mL suspension) in Healthy Adults
Dose* | AUC0-∞ (mcg• hr/mL) | Cmax (mcg/mL) †
Amoxicillin | Amoxicillin (±S.D.) | Amoxicillin (±S.D.)
400 mg (5 mL of suspension) | 17.1 (3.1) | 5.92 (1.62)
400 mg (1 chewable tablet) | 17.9 (2.4) | 5.18 (1.64)

* Administered at the start of a light meal.
† Mean values of 24 normal volunteers. Peak concentrations occurred approximately 1 hour after the dose.

Distribution: Amoxicillin diffuses readily into most body tissues and fluids, with the exception of brain and spinal fluid, except when meninges are inflamed. In blood serum, Amoxicillin is approximately 20% protein-bound. Following a 1-gram dose and utilizing a special skin window technique to determine levels of the antibiotic, it was noted that therapeutic levels were found in the interstitial fluid.
Metabolism and Excretion: The half-life of Amoxicillin is 61.3 minutes. Approximately 60% of an orally administered dose of Amoxicillin is excreted in the urine within 6 to 8 hours. Detectable serum levels are observed up to 8 hours after an orally administered dose of Amoxicillin. Since most of the Amoxicillin is excreted unchanged in the urine, its excretion can be delayed by concurrent administration of probenecid [see DRUG INTERACTIONS (7.1)].

12.4 Microbiology

Mechanism of Action
Amoxicillin is similar to penicillin in its bactericidal action against susceptible bacteria during the stage of active multiplication. It acts through the inhibition of cell wall biosynthesis that leads to the death of the bacteria.
Method of Resistance
Resistance to Amoxicillin is mediated primarily through enzymes called beta-lactamases that cleave the beta-lactam ring of Amoxicillin, rendering it inactive.

Amoxicillin has been shown to be active against most isolates of the bacteria listed below, both in vitro and in clinical infections as described in the INDICATIONS AND USAGE section.

Gram-Positive Bacteria | Gram-Negative Bacteria
Enterococcus faecalis Staphylococcus spp. Streptococcus pneumoniae alpha and β-hemolytic streptococci. | Escherichia coli Haemophilus influenzae Neisseria gonorrhoeae Proteus mirabilis Helicobacter pylori

Susceptibility Testing
For specific information regarding susceptibility test interpretive criteria and associated test methods and quality control standards recognized by FDA for this drug, please see: https://www.fda.gov/STIC.

13 NONCLINICAL TOXICOLOGY

13.1 Carcinogenesis, Mutagenesis, Impairment of Fertility

Long-term studies in animals have not been performed to evaluate carcinogenic potential. Studies to detect mutagenic potential of Amoxicillin alone have not been conducted; however, the following information is available from tests on a 4:1 mixture of Amoxicillin and potassium clavulanate. Amoxicillin and potassium clavulanate was non-mutagenic in the Ames bacterial mutation assay, and the yeast gene conversion assay. Amoxicillin and clavulanate potassium was weakly positive in the mouse lymphoma assay, but the trend toward increased mutation frequencies in this assay occurred at doses that were also associated with decreased cell survival. Amoxicillin and clavulanate potassium was negative in the mouse micronucleus test and in the dominant lethal assay in mice. Potassium clavulanate alone was tested in the Ames bacterial mutation assay and in the mouse micronucleus test, and was negative in each of these assays. In a multi-generation reproduction study in rats, no impairment of fertility or other adverse reproductive effects were seen at doses up to 500 mg/kg (approximately 2 times the 3 g human dose based on body surface area).

14 CLINICAL STUDIES

14.1 H. pylori Eradication to Reduce the Risk of Duodenal Ulcer Recurrence

Randomized, double-blind clinical studies performed in the United States in patients with H. pylori and duodenal ulcer disease (defined as an active ulcer or history of an ulcer within 1 year) evaluated the efficacy of lansoprazole in combination with Amoxicillin capsules and clarithromycin tablets as triple 14-day therapy, or in combination with Amoxicillin capsules as dual 14-day therapy, for the eradication of H. pylori. Based on the results of these studies, the safety and efficacy of 2 different eradication regimens were established: Triple therapy: Amoxicillin 1 gram twice daily/clarithromycin 500 mg twice daily/lansoprazole 30 mg twice daily (see Table 6). Dual therapy: Amoxicillin 1 gram three times daily/lansoprazole 30 mg three times daily (see Table 7). All treatments were for 14 days. H. pylori eradication was defined as 2 negative tests (culture and histology) at 4 to 6 weeks following the end of treatment. Triple therapy was shown to be more effective than all possible dual therapy combinations. Dual therapy was shown to be more effective than both monotherapies. Eradication of H. pylori has been shown to reduce the risk of duodenal ulcer recurrence.

Table 6. H. pylori Eradication Rates When Amoxicillin is Administered as Part of a Triple Therapy Regimen
Study | Triple Therapy | Triple Therapy
 | Evaluable Analysisa [95% Confidence Interval] (number of patients) | Intent-to-Treat Analysisb [95% Confidence Interval] (number of patients)
Study 1 | 92 [80 - 97.7] (n=48) | 86 [73.3 – 93.5] (n=55)
Study 2 | 86 [75.7 - 93.6] (n=66) | 83 [72 - 90.8] (n=70)

a This analysis was based on evaluable patients with confirmed duodenal ulcer (active or within 1 year) and H. pylori infection at baseline defined as at least 2 of 3 positive endoscopic tests from CLOtest®, histology, and/or culture. Patients were included in the analysis if they completed the study. Additionally, if patients dropped out of the study due to an adverse event related to the study drug, they were included in the analysis as failures of therapy.
b Patients were included in the analysis if they had documented H. pylori infection at baseline as defined above and had a confirmed duodenal ulcer (active or within 1 year). All dropouts were included as failures of therapy.

Table 7. H. pylori Eradication Rates When Amoxicillin is Administered as Part of a Dual Therapy Regimen
Study | Dual Therapy | Dual Therapy
 | Evaluable Analysisa [95% Confidence Interval] (number of patients) | Intent-to-Treat Analysisb [95% Confidence Interval] (number of patients)
Study 1 | 77 [62.5 - 87.2] (n=51) | 70 [56.8 – 81.2] (n=60)
Study 2 | 66 [51.9 - 77.5] (n=58) | 61 [48.5 - 72.9] (n=67)

a This analysis was based on evaluable patients with confirmed duodenal ulcer (active or within 1 year) and H. pylori infection at baseline defined as at least 2 of 3 positive endoscopic tests from CLOtest®, histology, and/or culture. Patients were included in the analysis if they completed the study. Additionally, if patients dropped out of the study due to an adverse event related to the study drug, they were included in the analysis as failures of therapy.
b Patients were included in the analysis if they had documented H. pylori infection at baseline as defined above and had a confirmed duodenal ulcer (active or within 1 year). All dropouts were included as failures of therapy.

15 REFERENCES

1. Swanson-Biearman B, Dean BS, Lopez G, Krenzelok EP. The effects of penicillin and cephalosporin ingestions in children less than six years of age.Vet Hum Toxicol. 1988; 30: 66-67

16 HOW SUPPLIED/STORAGE AND HANDLING

Amoxicillin for Oral Suspension, USP:Each 5 mL of reconstituted fruity-flavored suspension contains 125, 200, 250, or 400 mg Amoxicillin as the trihydrate.

Amoxicillin for Oral Suspension, USP 250 mg/5mL
80-mL bottle - NDC 68071-2364-8

Store at 20° to 25°C (68° to 77°F) [See USP Controlled Room Temperature]
Dispense in a tight, light-resistant container as defined in the USP using a child-resistant closure.

17.1 Information for Patients

- Patients should be advised that Amoxicillin for oral suspension may be taken every 8 hours or every 12 hours, depending on the dose prescribed.
- Patients should be counseled that antibacterial drugs, including Amoxicillin for oral suspension, should only be used to treat bacterial infections. They do not treat viral infections (e.g., the common cold). When Amoxicillin for oral suspension is prescribed to treat a bacterial infection, patients should be told that although it is common to feel better early in the course of therapy, the medication should be taken exactly as directed. Skipping doses or not completing the full course of therapy may: (1) decrease the effectiveness of the immediate treatment, and (2) increase the likelihood that bacteria will develop resistance and will not be treatable by Amoxicillin for oral suspension or other antibacterial drugs in the future.
- Patients should be counseled that diarrhea is a common problem caused by antibiotics, and it usually ends when the antibiotic is discontinued. Sometimes after starting treatment with antibiotics, patients can develop watery and bloody stools (with or without stomach cramps and fever) even as late as 2 or more months after having taken their last dose of the antibiotic. If this occurs, patients should contact their physician as soon as possible.
- Patients should be aware that Amoxicillin for oral suspension contains a penicillin class drug product that can cause allergic reactions in some individuals.

Distributed by:

West-Ward Pharmaceutical Corp.

Eatontown, NJ 07724 USA

Manufactured by:
HIKMA Pharmaceuticals
P.O. Box 182400
Amman 11118 – Jordan

Revised September 2018